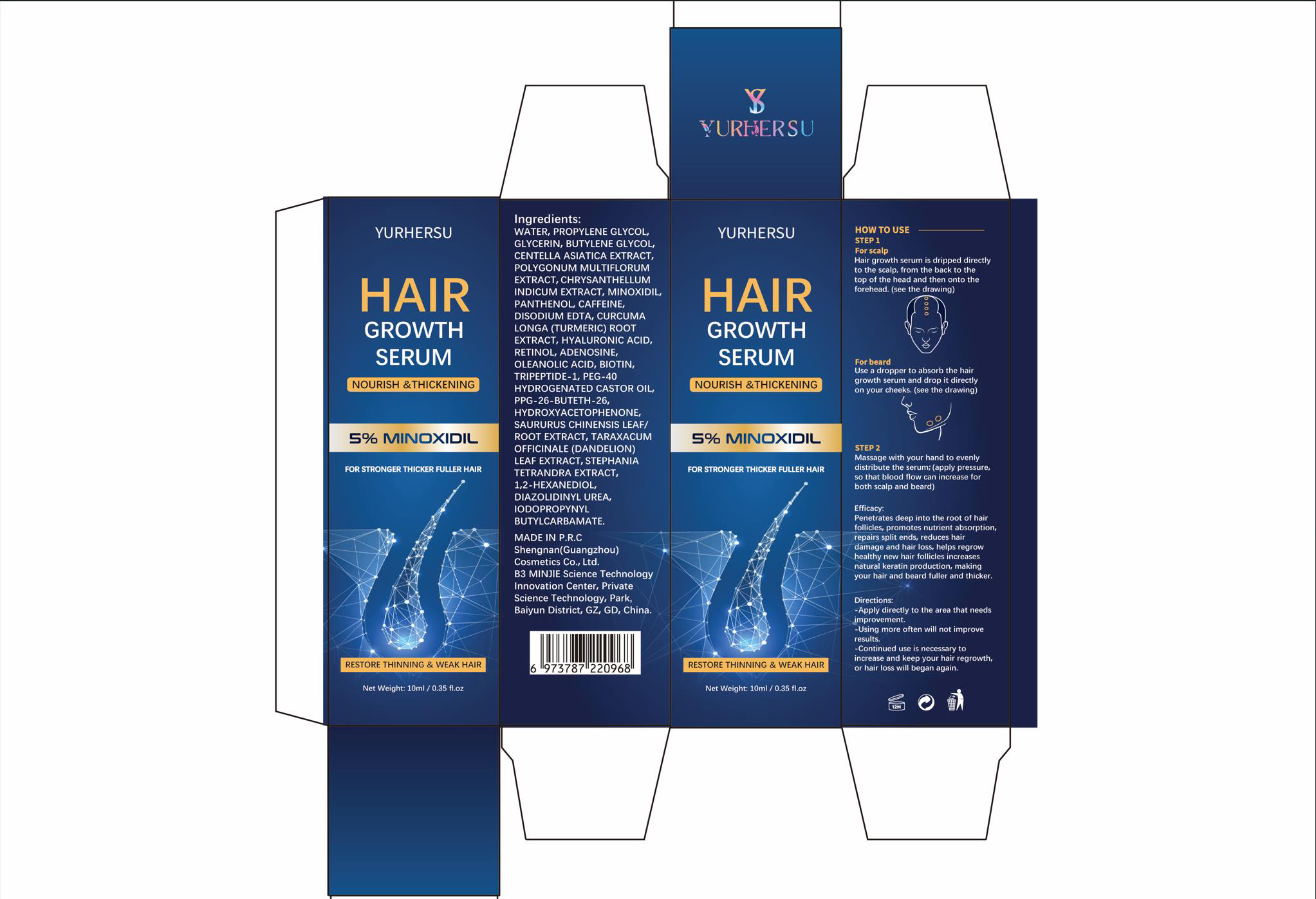 DRUG LABEL: HAIR GROWTH SERUM
NDC: 84019-401 | Form: LIQUID
Manufacturer: Shengnan (Guangzhou) Cosmetics Co., LTD
Category: otc | Type: HUMAN OTC DRUG LABEL
Date: 20240427

ACTIVE INGREDIENTS: MINOXIDIL 5 g/100 mL
INACTIVE INGREDIENTS: BUTYLENE GLYCOL; CAFFEINE BENZOATE; HYALURONIC ACID; TARAXACUM OFFICINALE LEAF; DIAZOLIDINYL UREA; PROPYLENE GLYCOL; CENTELLA ASIATICA TRITERPENOIDS; REYNOUTRIA MULTIFLORA WHOLE; ADENOSINE; THIOCTOYL TRIPEPTIDE-1; SAURURUS CHINENSIS WHOLE; STEPHANIA TETRANDRA WHOLE; 1,2-HEXANEDIOL; GLYCERIN; PANTHENOL; DISODIUM EDTA-COPPER; TURMERIC; RETINOL; IODOPROPYNYL BUTYLCARBAMATE; CHRYSANTHELLUM INDICUM TOP; OLEANOLIC ACID; BIOTIN; HYDROXYACETOPHENONE; PPG-26-BUTETH-26; WATER; POLYOXYL 40 HYDROGENATED CASTOR OIL

HAIR GROWTH SERUM

HAIR GROWTH SERUM

ACTIVE INGREDIENT

MINOXIDIL 5%

PURPOSE

FOR STRONGER THICKER FULLER HAIR

INDICATIONS AND USAGE

RESTORE THINNING & WEAK HAIR

WARNINGS

For external use only

DO NOT USE

Pregnant women and children are advised not to use, and do not use if there are wounds.

WHEN USING

Hair growth serum is dripped directlyto the scalp, from the back to thetop of the head and then onto theforehead. (see the drawing)。
For beard
Use a dropper to absorb the hairgrowth serum and drop it directlyon your cheeks. (see the drawing)
STEP 2
Massage with your hand to evenlydistribute the serum; (apply pressure,so that blood flow can increase forboth scalp and beard)
Efficacy:
Penetrates deep into the root of hairfollicles, promotes nutrient absorption,repairs split ends, reduces hairdamage and hair loss, helps regrowhealthy new hair follicles increasesnatural keratin production, makingyour hair and beard fuller and thicker.

STOP USE

If you experience any discomfort after use, please stop using and seek medical help promptly.

KEEP OUT OF REACH OF CHILDREN SECTION

DOSAGE AND ADMINISTRATION

Hair growth serum is dripped directlyto the scalp, from the back to thetop of the head and then onto theforehead. (see the drawing)。
For beard
Use a dropper to absorb the hairgrowth serum and drop it directlyon your cheeks. (see the drawing)
STEP 2
Massage with your hand to evenlydistribute the serum; (apply pressure,so that blood flow can increase forboth scalp and beard)
Efficacy:
Penetrates deep into the root of hairfollicles, promotes nutrient absorption,repairs split ends, reduces hairdamage and hair loss, helps regrowhealthy new hair follicles increasesnatural keratin production, makingyour hair and beard fuller and thicker.
Directions:
-Apply directly to the area that needsimprovement
-Using more often will not improve results.
-Continued use is necessary toincrease and keep your hair regrowth,or hair loss will began again.

STORAGE AND HANDLING

Store in a dark and cool place.

INACTIVE INGREDIENT

WATER
PROPYLENE GLYCOL
GLYCERIN
BUTYLENE GLYCOL
CENTELLA ASIATICA EXTRACT
POLYGONUM MULTIFLORUM EXTRACT
CHRYSANTHELLUM INDICUM EXTRACT
PANTHENOL
CAFFEINE
DISODIUM EDTA
CURCUMA LONGA (TURMERIC) ROOT EXTRACT
HYALURONIC ACID
RETINOL
ADENOSINE
OLEANOLIC ACID
BIOTIN
TRIPEPTIDE-1
PEG-40 HYDROGENATED CASTOR OIL
PPG-26-BUTETH-26
HYDROXYACETOPHENONE
SAURURUS CHINENSIS LEAF/ROOT EXTRACT
TARAXACUM OFFICINALE (DANDELION) LEAF EXTRACT
STEPHANIA TETRANDRA EXTRACT
1,2-HEXANEDIOL
DIAZOLIDINYL UREA
IODOPROPYNYL BUTYLCARBAMATE